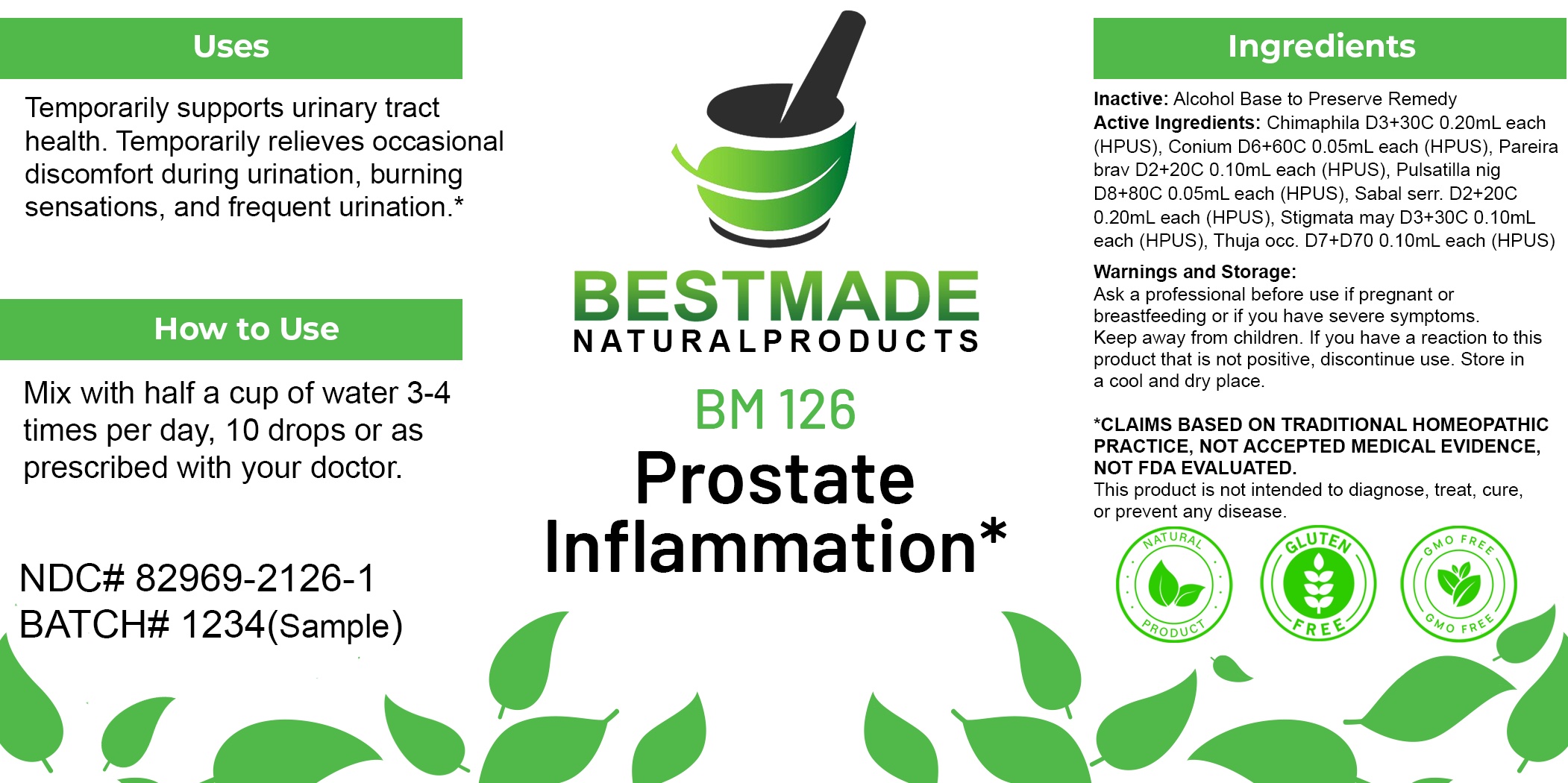 DRUG LABEL: Bestmade Natural Products BM126
NDC: 82969-2126 | Form: LIQUID
Manufacturer: Bestmade Natural Products
Category: homeopathic | Type: HUMAN OTC DRUG LABEL
Date: 20250210

ACTIVE INGREDIENTS: CORN SILK 30 [hp_C]/30 [hp_C]; SAW PALMETTO 30 [hp_C]/30 [hp_C]; CHONDRODENDRON TOMENTOSUM ROOT 30 [hp_C]/30 [hp_C]; THUJA OCCIDENTALIS LEAFY TWIG 30 [hp_C]/30 [hp_C]; PULSATILLA PRATENSIS WHOLE 30 [hp_C]/30 [hp_C]; CHIMAPHILA UMBELLATA WHOLE 30 [hp_C]/30 [hp_C]; CONIUM MACULATUM FLOWERING TOP 30 [hp_C]/30 [hp_C]
INACTIVE INGREDIENTS: ALCOHOL 30 [hp_C]/30 [hp_C]

BM126

DOSAGE AND ADMINISTRATION

How to Use

Mix with half a cup of water 3-4 times per day. Ages 12 or older, 10 drops. Ages 12-2, 5 drops. Ages 2 and under, consult your Doctor.

Inactive:

Alcohol Base to Preserve Product

ACTIVE INGREDIENTS

Chimaphila D3+30C 0.20mL each (HPUS), Conium D6+60C 0.05mL each (HPUS), Pareira brav D2+20C 0.10mL each (HPUS), Pulsatilla nig D8+80C 0.05mL each (HPUS), Sabal serr. D2+20C 0.20mL each (HPUS), Stigmata may D3+30C 0.10mL each (HPUS), Thuja occ. D7+D70 0.10mL each (HPUS)

Uses
Temporarily supports urinary tract health. Temporarily relieves occasional discomfort during urination, burning sensations, and frequent urination.*

Uses
Temporarily supports urinary tract health. Temporarily relieves occasional discomfort during urination, burning sensations, and frequent urination.*

KEEP OUT OF REACH OF CHILDREN

Warnings and Storage:

Ask a professional before use if pregnant or breastfeeding or if you have severe symptoms.

Keep away from children. If you have a reaction to this product that is not positive, discontinue use. Store in a cool and dry place

*CLAIMS BASED ON TRADITIONAL HOMEOPATHIC PRACTICE, NOT ACCEPTED MEDICAL EVIDENCE NOT FDA EVALUATED.
This product is not intended to diagnose, treat, cure, or prevent any disease.

Warnings and Storage:

Ask a professional before use if pregnant or breastfeeding or if you have severe symptoms.

Keep away from children. If you have a reaction to this product that is not positive, discontinue use. Store in a cool and dry place

*CLAIMS BASED ON TRADITIONAL HOMEOPATHIC PRACTICE, NOT ACCEPTED MEDICAL EVIDENCE NOT FDA EVALUATED.
This product is not intended to diagnose, treat, cure, or prevent any disease.

Entire package label